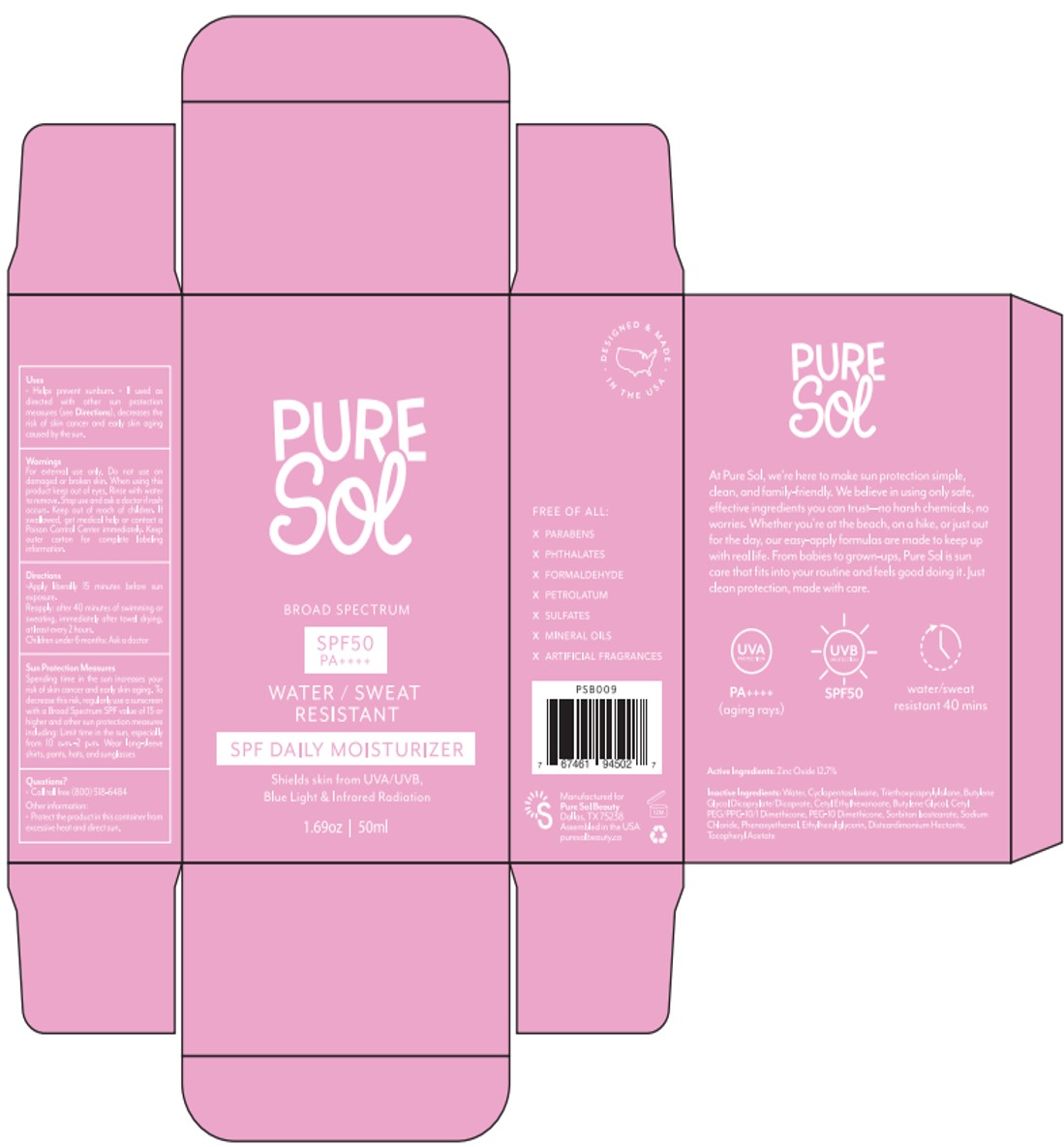 DRUG LABEL: PURE SOL SPF 50 Daily Moisturizer
NDC: 84090-001 | Form: LIQUID
Manufacturer: Brand 2022b LLC
Category: otc | Type: HUMAN OTC DRUG LABEL
Date: 20251004

ACTIVE INGREDIENTS: ZINC OXIDE 12.7 g/100 mL
INACTIVE INGREDIENTS: CETYL ETHYLHEXANOATE; ETHYLHEXYLGLYCERIN; TRIETHOXYCAPRYLYLSILANE; .ALPHA.-TOCOPHEROL ACETATE; PEG-10 DIMETHICONE (600 CST); PHENOXYETHANOL; CETYL PEG/PPG-10/1 DIMETHICONE (HLB 2); WATER; SORBITAN ISOSTEARATE; DISTEARDIMONIUM HECTORITE; BUTYLENE GLYCOL DICAPRYLATE/DICAPRATE; CYCLOMETHICONE 5; BUTYLENE GLYCOL; SODIUM CHLORIDE

84090-001-01. PURE SOL SPF 50 Daily Moisturizer-liquid-50ml

ACTIVE INGREDIENT

Zinc Oxide 12.5% Sunscreen

PURPOSE

Helps Prevent Sunburn
If used as directed with other sun protection measures (see Directions), decreases the risk of skin cancer and early skin aging caused by the sun.

WARNINGS

For external use only

Flammable: Contents under pressure. Do not puncture or incinerate. Do not store at temperatures above 120F. Do not use in the presence of a flame or spark or while smoking.

Do not use on damaged or broken skin

When using this product, keep away from face to avoid breathing it. Keep out of eyes

Rinse with water to remove.

Keep out of reach of children. If product is swallowed, get medical help or contact a poison Control Center right away

Stop use and ask a doctor if rash occurs

DOSAGE AND ADMINISTRATION

spray generously and spread evenly by hand 15 minutes before sun exposure
hold container 4 to 6 inches from the skin to apply
do not spray directly into face. Spray on hands then apply to face

Sun Protection Measures Spending time in the sun increases your risk of skin cancer and early skin aging. To decrease this risk, regularly use a sunscreen with a Broad-Spectrum SPF value of 15 or higher and other sun protection measures including:

• limit your time in the sun, especially from 10 a.m. – 2 p.m.

• wear long-sleeved shirts, pants, hats, and sunglasses

INACTIVE INGREDIENT

WATER
CYCLOPENTASILOXANE
TRIETHOXYCAPRYLYLSILANE
BUTYLENE GLYCOL DICAPRYLATE/DICAPRATE
CETYL ETHYLHEXANOATE
BUTYLENE GLYCOL
CETYL PEG/PPG-10/1 DIMETHICONE
PEG-10 DIMETHICONE
SORBITAN ISOSTEARATE
SODIUM CHLORIDE
PHENOXYETHANOL
ETHYLHEXYLGLYCERIN
DISTEARDIMONIUM HECTORITE
WATER
TOCOPHERYL ACETATE